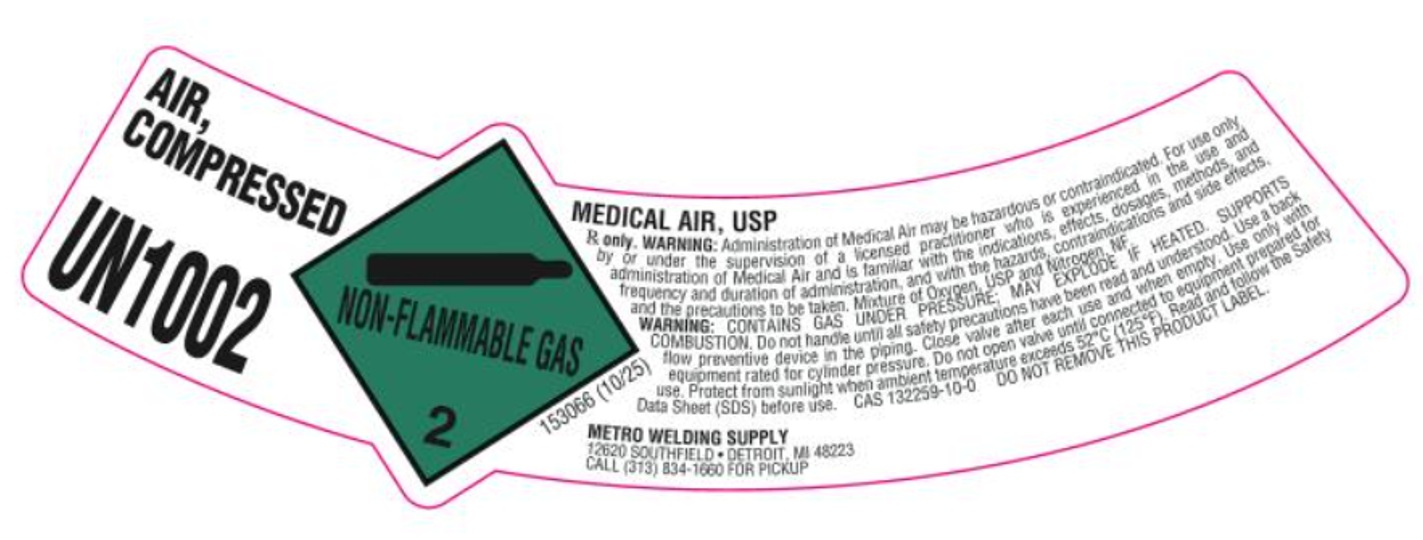 DRUG LABEL: Air
NDC: 62273-013 | Form: GAS
Manufacturer: Metro Welding Supply Corporation
Category: animal | Type: PRESCRIPTION ANIMAL DRUG LABEL
Date: 20251020

ACTIVE INGREDIENTS: Air 1000 mL/1 L

Reconstituted Air

PACKAGE LABEL

AIR, COMPRESSED
UN1002
MEDICAL AIR, USP
Rx only. WARNING: Administration of Medical Air may be hazardous or contraindicated. For use only by or under the supervision of a licensed practitioner who is experienced in the use and administration of Medical Air and is familiar with the indications, effects, dosages, methods, and frequency and duration of administration, and with the hazards, contraindications and side effects, and the precautions to be taken. Mixture of Oxygen, USP and Nitrogen, NF.
WARNING: CONTAINS GAS UNDER PRESSURE; MAY EXPLODE IF HEATED. SUPPORTS COMBUSTION. Do not handle until all safety precautions have been read and understood. Use a back flow preventive device in the piping. Close valve after each use and when empty. Use only with equipment rated for cylinder pressure. Do not open valve until connected to equipment prepared for use. Protect from sunlight when ambient temperature exceeds 52 C (125 F). Read and follow the Safety Data Sheet (SDS) before use.
CAS 132259-10-0 DO NOT REMOVE THIS PRODUCT LABEL.
METRO WELDING SUPPLY
12620 SOUTHFIELD DETROIT, MI 48223
CALL (313) 834-1660 FOR PICKUP